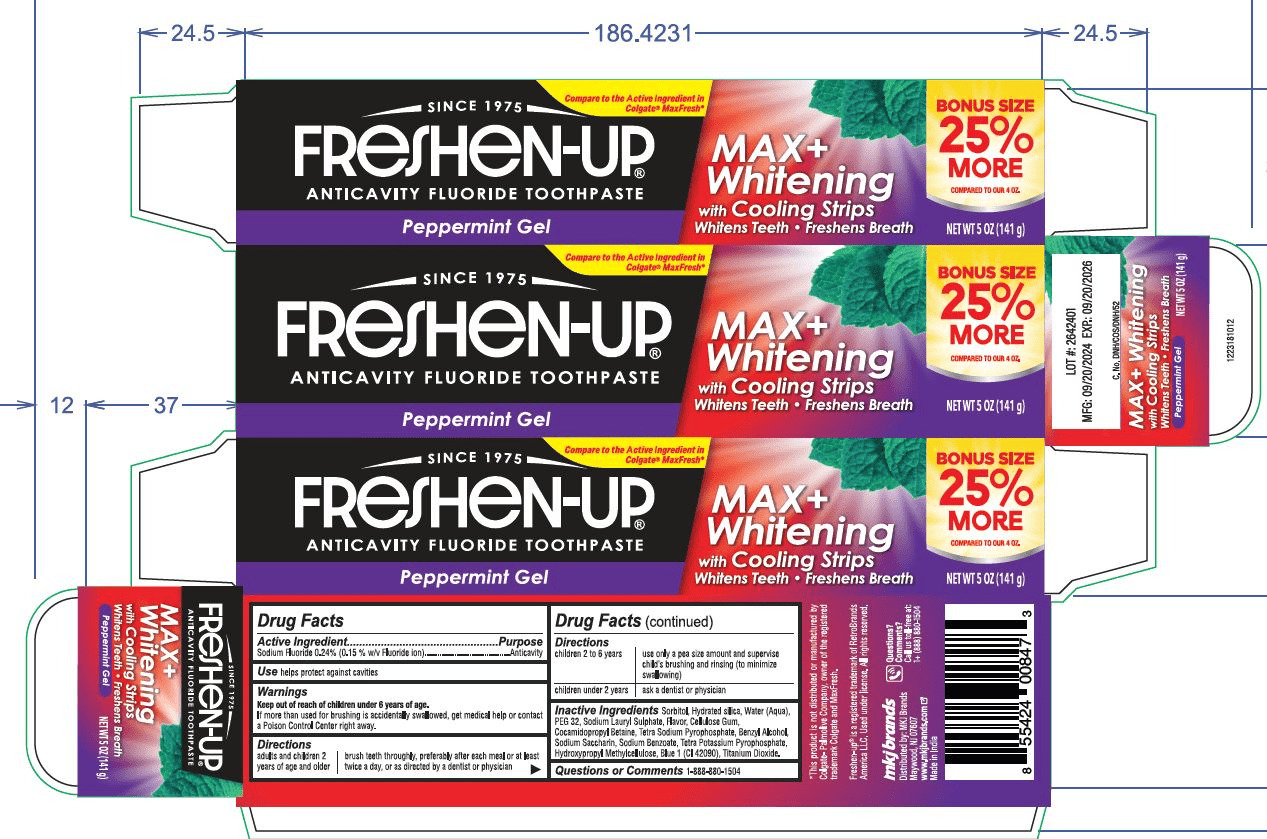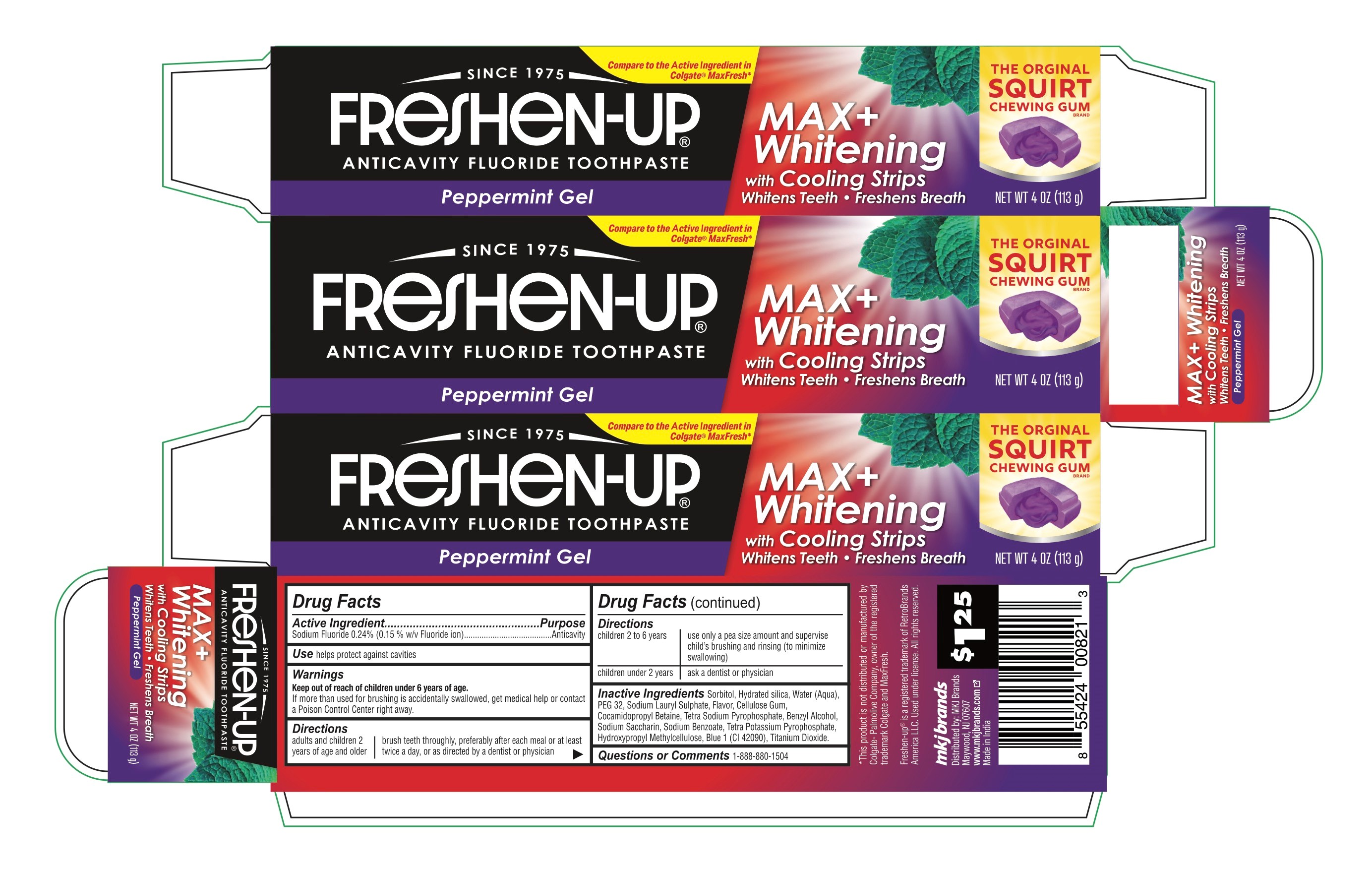 DRUG LABEL: Freshen Up
NDC: 77782-001 | Form: GEL, DENTIFRICE
Manufacturer: MKJ BRANDS LLC
Category: otc | Type: HUMAN OTC DRUG LABEL
Date: 20250901

ACTIVE INGREDIENTS: SODIUM FLUORIDE 24 mg/100 g
INACTIVE INGREDIENTS: HYDROXYPROPYL METHYLCELLULOSE; BENZYL ALCOHOL; SODIUM LAURYL SULFATE; SODIUM BENZOATE; SORBITOL; WATER; HYDRATED SILICA; PEG-32; SACCHARIN SODIUM; CELLULOSE GUM; TETRASODIUM PYROPHOSPHATE; COCAMIDOPROPYL BETAINE; TETRAPOTASSIUM PYROPHOSPHATE; FD&C BLUE NO. 1; TITANIUM DIOXIDE

Freshen Up Anticavity Fluoride Toothpaste Max+ Whitening

Drug Facts

Active ingredient

Sodium fluoride 0.24% (0.15% w/v fluoride ion)

Purpose

Anticavity

Use

helps protect against cavities

Warnings

Keep out of reach of children under 6 years of age.If more than used for brushing is accidentally swallowed, get medical help or contact a Poison Control Center right away.

Directions

adults and children 2 years of age and older | brush teeth thoroughly, preferably after each meal or at least twice a day, or as directed by a dentist or physician
children 2 to 6 years | use only a pea sized amount and supervise child's brushing and rinsing (to minimize swallowing)
children under 2 years | ask a dentist or physician

Inactive ingredients

sorbitol, water, hydrated silica, PEG-32, sodium lauryl sulfate, flavor, tetrasodium pyrophosphate, cellulose gum, cocamidopropyl betaine, sodium saccharin,hydroxypropyl methylcellulose, FD&C blue no. 1,titanium dioxide, benzyl alcohol,tetra potassium pyrophosphate

Questions?

1-888-880-1504

Dist. by:
MKJ Brands